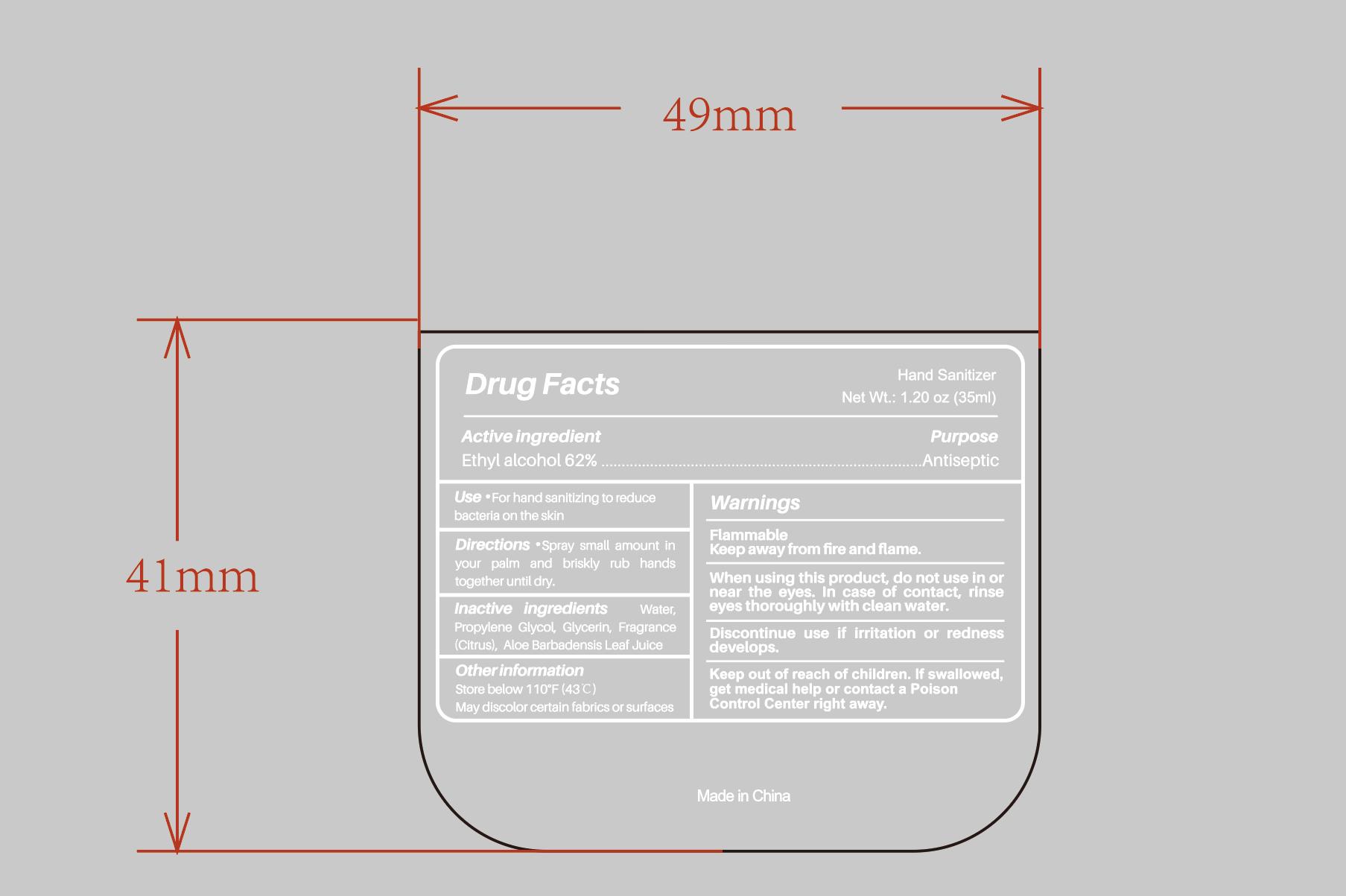 DRUG LABEL: Hand Sanitizer
NDC: 87001-006 | Form: LIQUID
Manufacturer: HAIAN KANGRUI TEXTILE CO., LTD.
Category: otc | Type: HUMAN OTC DRUG LABEL
Date: 20251229

ACTIVE INGREDIENTS: ALCOHOL 62 mL/100 mL
INACTIVE INGREDIENTS: GLYCERIN; ALOE BARBADENSIS LEAF JUICE; ALOE VERA LEAF; WATER

87001-006

Active Ingredient

Ethyl Alcohol 62%

Purpose

Antiseptic

Uses

For hand sanitizing to reduce bacteria on the skin.

Warnings

Flammable

Keep away from fire and flame.

When using this product，

do not use in or near the eyes.In case of contact，rinse eyes thoroughly with water.

Discontinue use

if irritation or redness develops.

Keep out of reach of children.

If swallowed, get medical help or contact a Poison Control Center right away.

Directions

Spray small amount in your palm and briskly rub hands together until dry.

Inactive ingredients

Water, Propylene Glycol, Glycerin, Fragrance (Citrus), Aloe Barbadensis Leaf Juice